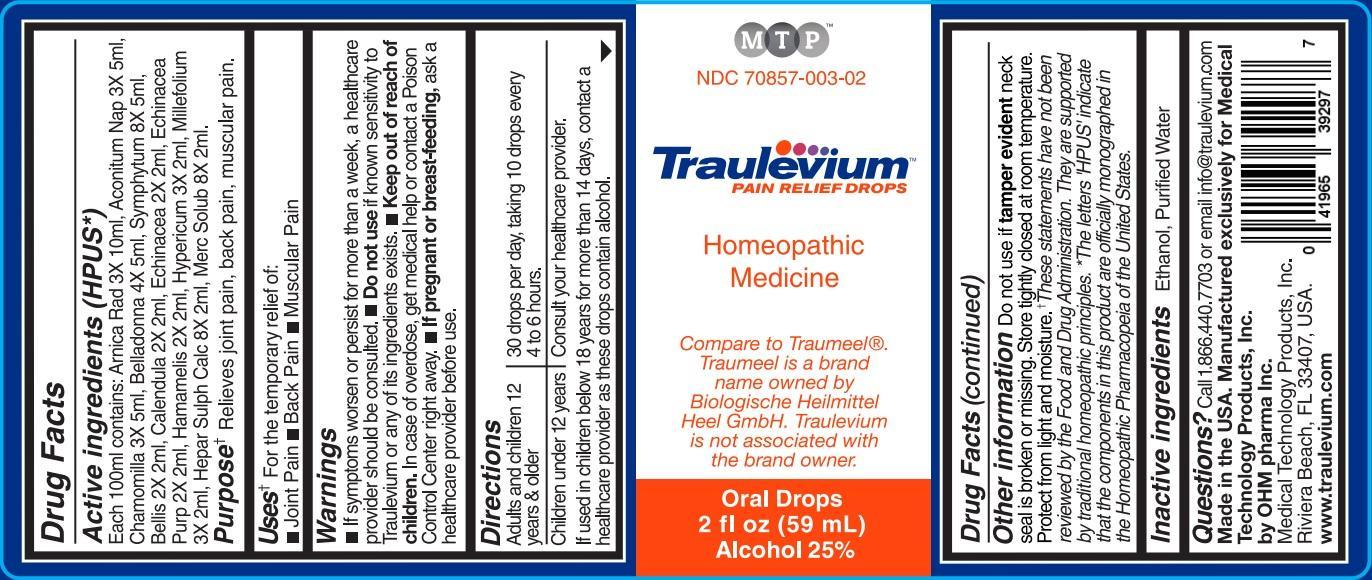 DRUG LABEL: TRAULEVIUM


NDC: 70857-003 | Form: LIQUID
Manufacturer: Medical Technology Products, Inc.
Category: homeopathic | Type: HUMAN OTC DRUG LABEL
Date: 20211229

ACTIVE INGREDIENTS: ARNICA MONTANA ROOT 3 [hp_X]/59 mL; ACONITUM NAPELLUS 3 [hp_X]/59 mL; MATRICARIA RECUTITA 3 [hp_X]/59 mL; ATROPA BELLADONNA 4 [hp_X]/59 mL; COMFREY ROOT 8 [hp_X]/59 mL; BELLIS PERENNIS 2 [hp_X]/59 mL; CALENDULA OFFICINALIS FLOWERING TOP 2 [hp_X]/59 mL; ECHINACEA ANGUSTIFOLIA 2 [hp_X]/59 mL; ECHINACEA PURPUREA 2 [hp_X]/59 mL; HAMAMELIS VIRGINIANA ROOT BARK/STEM BARK 2 [hp_X]/59 mL; HYPERICUM PERFORATUM 3 [hp_X]/59 mL; ACHILLEA MILLEFOLIUM 3 [hp_X]/59 mL; CALCIUM SULFIDE 8 [hp_X]/59 mL; MERCURIUS SOLUBILIS 8 [hp_X]/59 mL
INACTIVE INGREDIENTS: ALCOHOL; WATER

TRAULEVIUM PAIN RELIEF DROPS

ACTIVE INGREDIENTS

Active ingredients (HPUS*)

Each 100ml contains: Arnica Rad 3X 10ml, Aconitum Nap 3X 5ml, Chamomilla 3X 5ml, Belladonna 4X 5ml, Symphytum 8X 5ml, Bellis 2X 2ml, Calendula 2X 2ml, Echinacea 2X 2ml, Echinacea Purp 2X 2ml, Hamamelis 2X 2ml, Hypericum 3X 2ml, Millefolium 3X 2ml, Hepar Sulph Calc 8X 2ml, Merc Solub 8X 2ml.

Purpose** Relieves joint pain, back pain, muscular pain.

USES

For the temporary relief of:

- Joint Pain
- Back Pain
- Muscular Pain

WARNINGS

- If symptoms worsen or persist for more than a week, a healthcare provider should be consulted.
- Do not use if known sensitivity to Traulevium or any of its ingredients exists.
- Keep out of reach of children. In case of overdose, get medical help or contact a Poison Control Center right away.
- If pregnant or breast-feeding, ask a healthcare provider before use.

keep out of reach of children

DIRECTIONS

Adults and children 12 years & older | 30 drops per day, taking 10 drops every 4 to 6 hours.
Children under 12 years | Consult your healthcare provider.

If used in children below 18 years for more than 14 days, contact a healthcare provider as these drops contain alcohol.

OTHER INFORMATION

Do not use if tamper evident neck seal is broken or missing. Store tightly closed at room temperature. Protect from light and moisture.

**These statements have not been reviewed by the Food and Drug Administration. They are supported by traditional homeopathic principles.

*The letters 'HPUS' indicate that the components in this product are officially monographed in the Homeopathic Pharmacopeia of the United States.

INACTIVE INGREDIENTS

Ethanol, Purified Water

QUESTIONS

Call 1.866.440.7703 or email info@traulevium.com

Made in the USA. Manufactured exclusively for Medical Technology Products, Inc. by OHM pharma Inc.

Medical Technology Products, Inc.

Riviera Beach, FL 33407, USA.

www.traulevium.com

PACKAGE LABEL

MTP

NDC 70857-003-02

Traulevium™

PAIN RELIEF DROPS

Homeopathic Medicine

Compare to Traumeel®. Traumeel is a brand name owned by Biologische Heilmittel Heel GmbH. Traulevium is not associated with the brand owner.

Oral Drops

2 fl oz (59 mL)

Alcohol 25%

PURPOSE

Pain Relief Drops